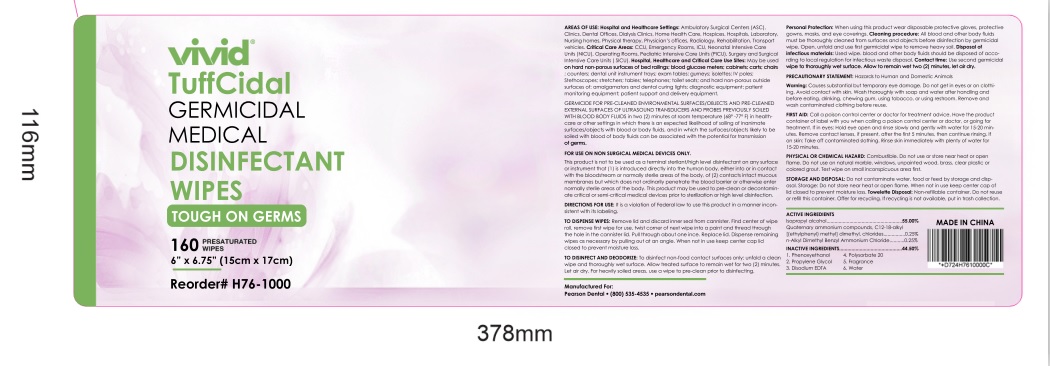 DRUG LABEL: Disinfecting Wipes
NDC: 80707-301 | Form: CLOTH
Manufacturer: Hangzhou Muzi Commodity Co., Ltd
Category: otc | Type: HUMAN OTC DRUG LABEL
Date: 20201218

ACTIVE INGREDIENTS: ISOPROPYL ALCOHOL 1 mL/1 1
INACTIVE INGREDIENTS: PHENOXYETHANOL; PROPYLENE GLYCOL; EDETATE DISODIUM ANHYDROUS; FRAGRANCE CLEAN ORC0600327; 3-CHLORO-2-HYDROXYPROPYLCOCOALKYLDIMETHYLAMMONIUM CHLORIDE; N-ALKYL DIMETHYL BENZYL AMMONIUM CHLORIDE (C12-C18); WATER; POLYSORBATE 20

Disinfecting Wipes

Disinfecting Wipes

Active Ingredient(s)

Isopropyl alcohol 1mL/pcs. Purpose: Antiseptic

Purpose

Antiseptic, Disinfecting Wipes

Use

Disinfecting Wipes to help reduce bacteria that potentially can cause disease. For use when soap and water are not available.

Warnings

For external use only. Flammable. Keep away from heat or flame

Do not use

- in children less than 2 months of age
- on open skin wounds

When using this product keep out of eyes, ears, and mouth. In case of contact with eyes, rinse eyes thoroughly with water.
Stop use and ask a doctor if irritation or rash occurs. These may be signs of a serious condition.
Keep out of reach of children. If swallowed, get medical help or contact a Poison Control Center right away.

Stop use and ask a doctor if irritation or rash occurs. These may be signs of a serious condition.

Keep out of reach of children. If swallowed, get medical help or contact a Poison Control Center right away.

Directions

- Wipe the surface of the skin and let it dry naturally.
- Supervise children under 6 years of age when using this product to avoid swallowing.

Other information

- Store between 15-30C (59-86F)
- Avoid freezing and excessive heat above 40C (104F)

Inactive ingredients

Quaternary ammonium compounds,C12-18-alkyl[(ethylphenyl) methyl] dimethyl,chlorides
n-Alkyl Dimethyl Benzyl Ammonium Chloride
Water
Phenoxyethanol
Propylene Glycol
Disodium EDTA
Polysorbate 20
Fragrance